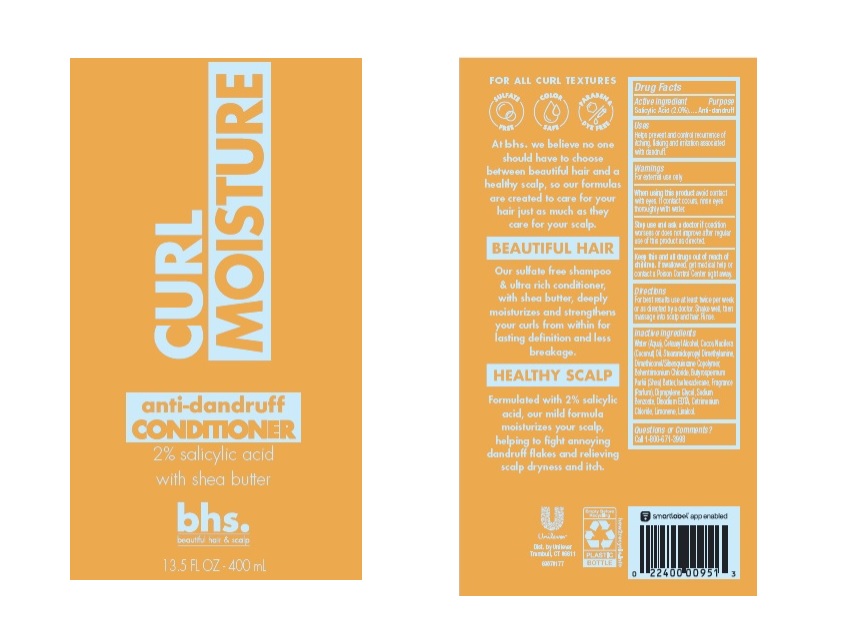 DRUG LABEL: bhs beautiful hair and scalp
NDC: 64942-2058 | Form: LIQUID
Manufacturer: Conopco, Inc. d/b/a/ Unilever
Category: otc | Type: HUMAN OTC DRUG LABEL
Date: 20241107

ACTIVE INGREDIENTS: SALICYLIC ACID 2 g/100 mL
INACTIVE INGREDIENTS: ISOHEXADECANE; SODIUM BENZOATE; SHEA BUTTER; STEARAMIDOPROPYL DIMETHYLAMINE; LIMONENE, (+)-; WATER; CETOSTEARYL ALCOHOL; BEHENTRIMONIUM CHLORIDE; COCONUT OIL; DIPROPYLENE GLYCOL; EDETATE DISODIUM ANHYDROUS; CETRIMONIUM CHLORIDE; LINALOOL, (+/-)-

bhs. beautiful hair & scalp Curl Moisture Anti-dandruff Conditioner

Drug Facts

Active ingredient

Salicylic Acid (2.0%)

Purpose

Anti-dandruff

Use

Helps prevent and control recurrence of itching, flaking and irritation associated with dandruff.

Warnings

For external use only
When using this product avoid contact with eyes. If contact occurs, rinse eyes thoroughtly with water.
Stop use and ask a doctor if condition worsens or does not improve after regular use of this product as directed.

KEEP OUT OF REACH OF CHILDREN

Keep this and all drugs out of reach of children.

If swallowed, get medical help or contact a Poison Control Center right away.

Directions

For best results use at least twice per week or as directed by a doctor. Shake well, then massage into scalp and hair. Rinse.

Inactive Ingredients

Water (Aqua), Cetearyl Alcohol, Cocos Nucifera (Coconut) Oil, Stearamidopropyl Dimethylamine, Dimethiconol/Silsesquioxane Copolymer, Behentrimonium Chloride, Butyrospermum Parkii (Shea) Butter, Isohexadecan, Fragrance (Parfum), Dipropylene Glycol, Sodium Benzoate, Disodium EDTA, Cetrimonium Chloride, Limonene, Linalool.

Questions or comments?

Call 1-800-671-3998